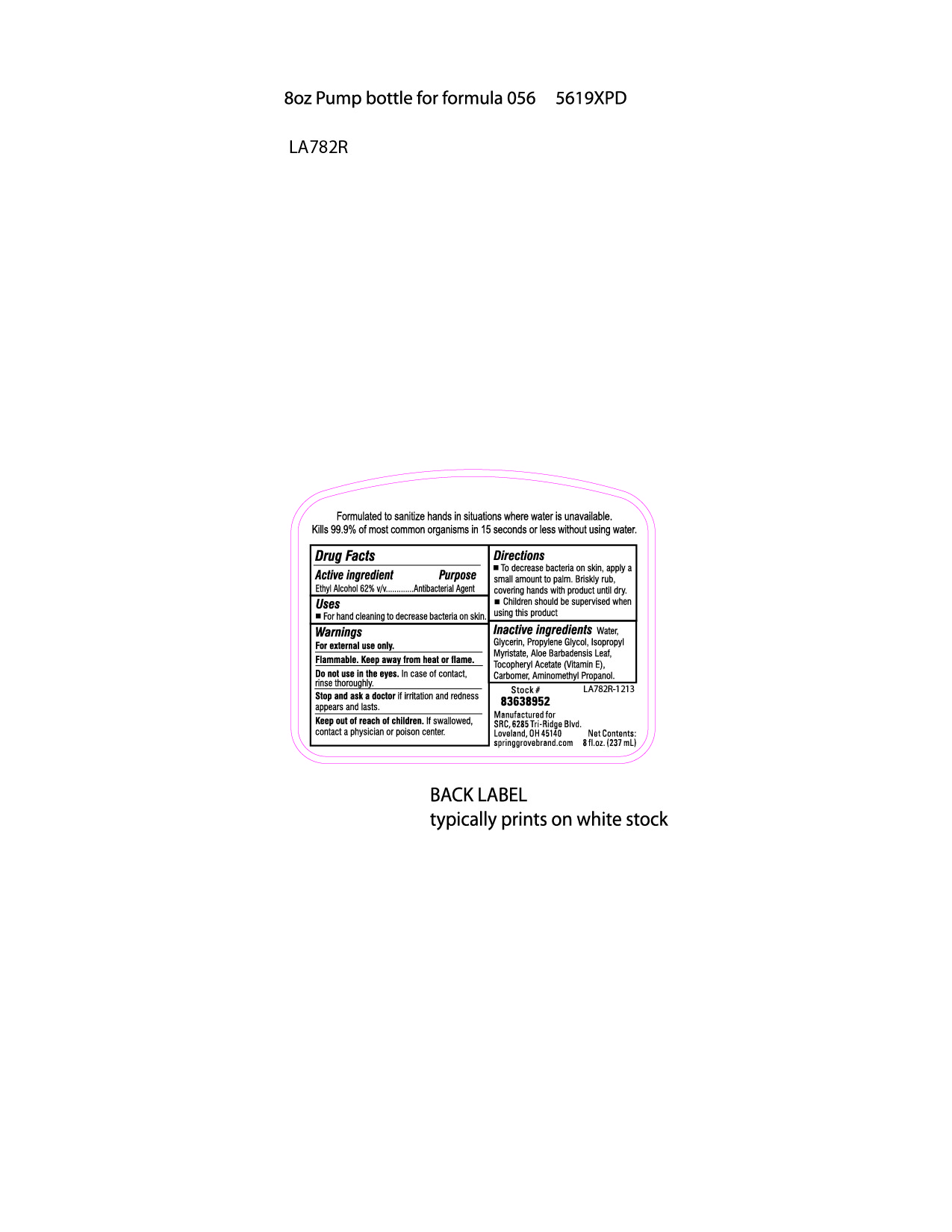 DRUG LABEL: Spring Grove Unscented Hand Sanitizer
NDC: 61827-056 | Form: SOLUTION
Manufacturer: Saalfeld Paper
Category: otc | Type: HUMAN OTC DRUG LABEL
Date: 20140129

ACTIVE INGREDIENTS: ALCOHOL 62.5 mL/100 mL
INACTIVE INGREDIENTS: POLYACRYLIC ACID (250000 MW); WATER; GLYCERIN; PROPYLENE GLYCOL; ISOPROPYL MYRISTATE; AMINOMETHYLPROPANOL; ALOE VERA LEAF; ALPHA-TOCOPHEROL ACETATE

Spring Grove Unscented Hand Sanitizer

ACTIVE INGREDIENT

Ethyl Alcohol 62% v/v.......Antibacterial Agent

INACTIVE INGREDIENT

Water, Glycerin, Propylene Glycol, Isopropyl Myristate, Aloe Barbadensis Leaf, Tocopheryl Acetate (Vitamin E), Carbomer, Aminomethyl Propanol.

PURPOSE

For hand cleaning to decrease bacteria on skin.

WARNINGS

For external use only.

Flammable. Keep away from heat or flame.

Do not use in the eyes. In case of contact, rinse thoroughly.

Stop and ask a doctor if irritation and redness appears and lasts.

Keep out of reach of children. If swallowed, contact a physician or poison center.

DOSAGE AND ADMINISTRATION

To decrease bacteria on skin, apply a small amount to palm. Briskly rub, covering hands with product until dry. Children should be supervised when using this product.

INDICATIONS AND USAGE

For hand cleaning to decrease bacteria on skin.

Do not use in the eyes. In case of contact, rinse thoroughly.

Stop and ask a doctor if irritation and redness appears and lasts.

Keep out of reach of children. If swallowed, contact a physician or poison center.

Keep out of reach of children. If swallowed, contact a physician or poision center.

PACKAGE LABEL

61827-056-08.jpg